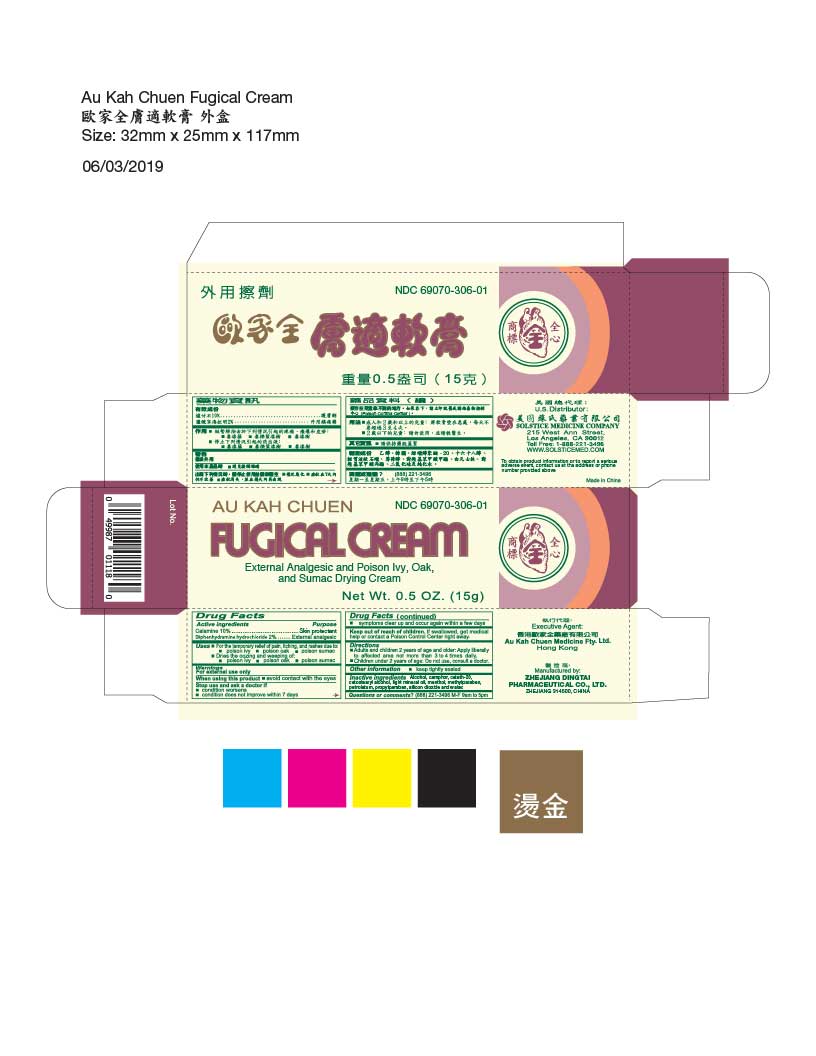 DRUG LABEL: Au Kah Chuen Fugical
NDC: 69070-306 | Form: CREAM
Manufacturer: Zhejiang Dingtai Pharmaceutical Co., Ltd
Category: otc | Type: HUMAN OTC DRUG LABEL
Date: 20251110

ACTIVE INGREDIENTS: ZINC OXIDE 9.95 g/100 g; FERRIC OXIDE RED 0.05 g/100 g; DIPHENHYDRAMINE HYDROCHLORIDE 2 g/100 g
INACTIVE INGREDIENTS: ALCOHOL; CAMPHOR (SYNTHETIC); CETETH-20; CETOSTEARYL ALCOHOL; LIGHT MINERAL OIL; MENTHOL; METHYLPARABEN; PETROLATUM; PROPYLPARABEN; SILICON DIOXIDE; WATER

Drug Facts

Active ingredient
Calamine 10%
Diphenhydramine hydrochloride 2%

Purpose
Skin protectant
External analgesic

Uses
For the temporary relief of pain, itching, and rushes due to:
poison ivy
poison oak
poison sumac

Dries the oozing and weeping of:
poison ivy
poison oak
poison sumac

Warnings
For external use only

When using this product
avoid contact with the eyes

Stop use and ask a doctor if
conditions worsens
condition does not improve within 7 days
symptoms clear up and occur again within a few days

Keep out of reach of children.If swallowed, get medical help or contact a Poison Control Center right away.

Directions
Adults and children 2 years of age or older: Apply liberally to affected area not more than 3 to 4 times daily.
Children under 2 years: Do not use, consult a doctor

Other information
keep tightly sealed

INACTIVE INGREDIENT

Inactive ingredientsAlcohol, camphor, ceteth-20, cetostearyl alcohol, light mineral oil, menthol, methylparaben, petrolatum, propylparaben, silicon dioxide and water.

Questions or comments?(888) 221-3496 M-F 9am-5pm
you may also report serious side effects to this phone number

PACKAGE LABEL

Au Kah Chuen Fugical Cream
Calamine 10%
Diphenhydramine hydrochloride 2%
External Analgesic and Poison Ivy, Oak, and Sumac Drying Cream
Net Wt. 0.5 oz (15 g)
NDC 69070-306-01